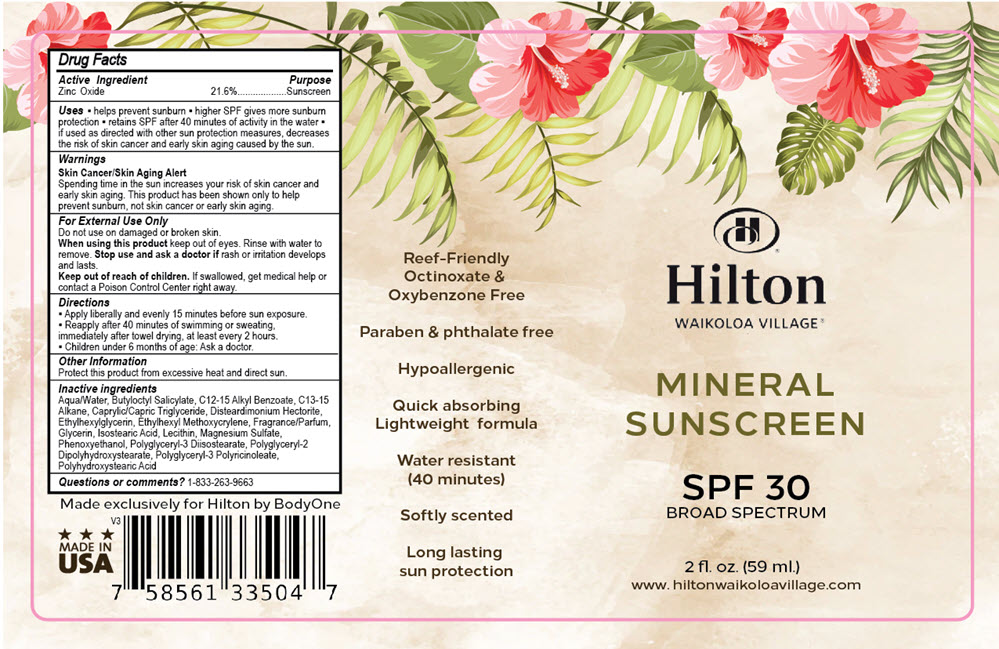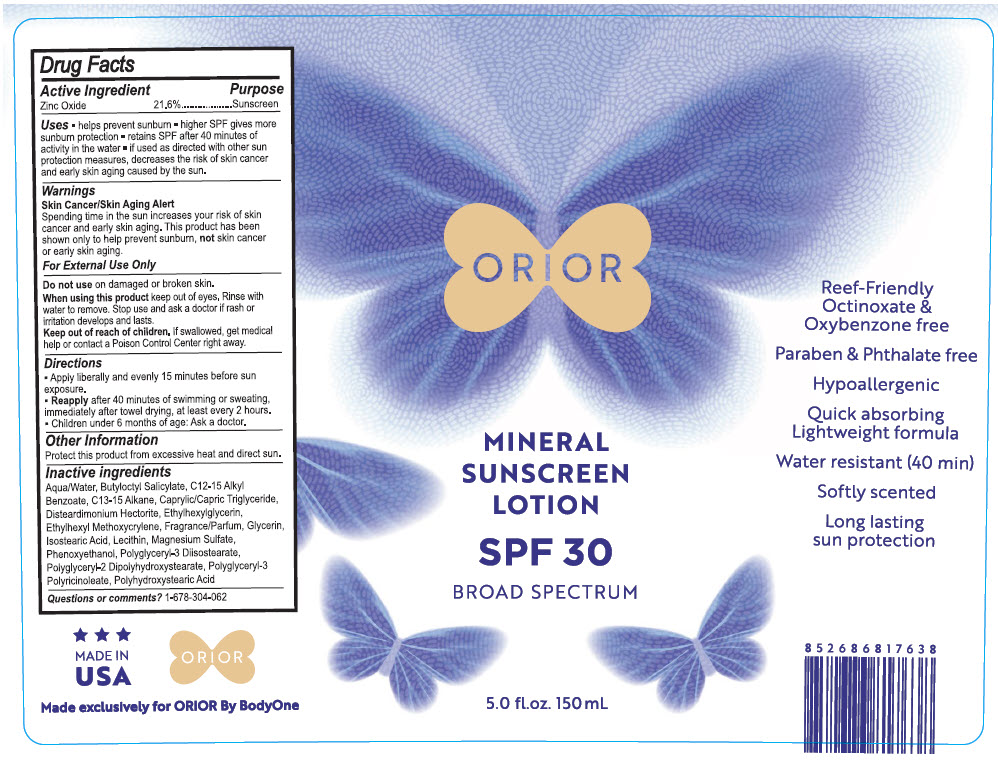 DRUG LABEL: Hilton SPF 30 Mineral Sunscreen
NDC: 73563-335 | Form: CREAM
Manufacturer: Body One, LLC
Category: otc | Type: HUMAN OTC DRUG LABEL
Date: 20230522

ACTIVE INGREDIENTS: ZINC OXIDE 21.6 g/100 mL
INACTIVE INGREDIENTS: WATER; MAGNESIUM SULFATE, UNSPECIFIED FORM; GLYCERIN; PHENOXYETHANOL; GUAIETOLIN, (S)-; POLYGLYCERYL-2 DIPOLYHYDROXYSTEARATE; BUTYLOCTYL SALICYLATE; C13-15 Alkane; MEDIUM-CHAIN TRIGLYCERIDES; ALKYL (C12-15) BENZOATE; ETHYLHEXYL METHOXYCRYLENE; POLYHYDROXYSTEARIC ACID (2300 MW); POLYGLYCERYL-3 PENTARICINOLEATE; ISOSTEARIC ACID; HYDROGENATED SOYBEAN LECITHIN; DISTEARDIMONIUM HECTORITE; LINALYL ACETATE; PHENYLETHYL ALCOHOL; ETHYL LINALOOL; TETRAHYDROLINALOOL

SPF 30 Mineral Sunscreen

Drug Facts

Active Ingredient

Zinc Oxide 21.6%

Purpose

Sunscreen

Uses

- Helps prevent sunburn.
- higher SPF five more sunburn protection
- retains SPF after 40 minutes of activity in the water
- If used as directed with other sun protection measures, decreases the risk of skin cancer and early skin aging caused by the sun.

Warnings

Skin Cancer/Skin Aging Alert

Spending time in the sun increases your risk of skin cancer and early skin aging. This product has been shown only to help prevent sunburn, not skin cancer of early skin aging.

For External Use Only

Do not use on damaged or broken skin.

When using this product keep out of eyes. Rinse with water to removed. Stop use and ask a doctor if rash of irritation develops and lasts.

Keep out of reach of Children. If swallowed, get medical help or contact a Poison Control Center right away.

Directions

- Apply liberally and evenly 15 minutes before sun exposure.
- Reapply after 40 minutes of swimming or sweating, immediately after towel drying, at least every 2 hours.

Children under 6 months of age: Ask a doctor.

Other Information

Protect this product from excessive heat and direct sun.

Inactive ingredients

Aqua/water, ButylOctyl Salicylate, C12-15 Alkyl Benzoate, Caprylic/Capric Triglyceride, Disteardimmonium Hectorite, EthylHexylglycerin, EthylhexylMethoxycrylene, Fragrance, Glycerine, Isostearic Acid, Lecithin, Magnesium Sulfate, Phenoxyethanol, Polyglyceryl-3 Diisostearate, Polyglyceryl-2 Dipolyhydroxystearate, Polyglyceryl-3 Polyricinoleate, Polyhydroxystearic Acid.

Questions or comments?

1-833-263-9663

PRINCIPAL DISPLAY PANEL - 59 ml. Bottle Label

Hilton
WAIKOLOA VILLAGE®

MINERAL
SUNSCREEN

SPF 30
BROAD SPECTRUM

2 fl. oz. (59 ml.)
www.hiltonwaikoloavillage.com

PRINCIPAL DISPLAY PANEL - 150 mL Bottle Label

ORIOR

MINERAL
SUNSCREEN
LOTION

SPF 30
BROAD SPECTRUM

5.0 fl.oz. 150 mL